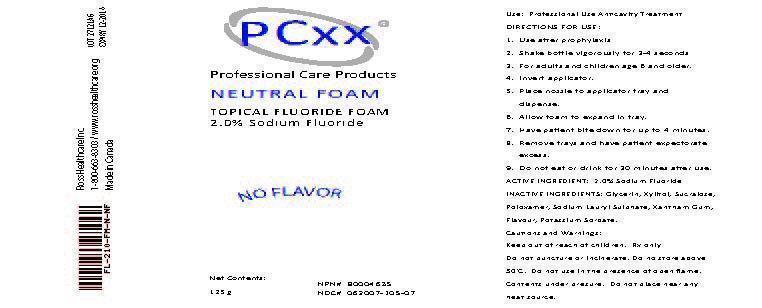 DRUG LABEL: PCxx
NDC: 62007-105 | Form: AEROSOL, FOAM
Manufacturer: Ross Healthcare Inc.
Category: prescription | Type: HUMAN PRESCRIPTION DRUG LABEL
Date: 20121217

ACTIVE INGREDIENTS: SODIUM FLUORIDE 2.5 g/125 g
INACTIVE INGREDIENTS: GLYCERIN; XYLITOL; SUCRALOSE; POLOXAMER 407; SODIUM LAURYL SULFATE; XANTHAN GUM; POTASSIUM SORBATE

Active Ingredient

ACTIVE INGREDIENT: 2.0% Sodium Fluoride

Use

Use: Professional Use Anticavity Treatment

Keep Out Of Reach Of Children

Use

Use: Professional Use Anticavity Treatment

Cautions and Warnings

Keep out of reach of children. Rx only. Do not puncture or incinerate. Do not store above 50 degrees C. Do not use in the presence of open flame. Contents under pressure. Do not place near any heat source.

Directions For Use

1. Use after prophylaxis.
2. Shake bottle vigorously for 3-4 seconds.
3. For adults and children age 6 and older.
4. Invert applicator.
5. Place nozzle to applicator tray and dispense.
6. Allow foam to expand in tray.
7. Have patient bite down for up to 4 minutes.
8. Remove trays and have patient expectorate excess.
9. Do not eat or drink for 30 minutes after use.

Inactive Ingredients

INACTIVE INGREDIENTS: Glycerin, Xylitol, Sucralose, Poloxamer, Sodium Lauryl Sulphate, Xantham Gum, Flavour, Potassium Sorbate.

Product Label

PCxx
Professional Care Products
NEUTRAL FOAM
TOPICAL FLUORIDE FOAM
2.0% Sodium Fluoride
NO FLAVOR
Net Contents: 125 g
NPN# 800004635
NDC# 062007-105-07
Ross Healthcare Inc. 1-800-663-8303 / www.rosshealthcare.org
Made in Canada
LOT 27121A6
EXPIRY 12-2014